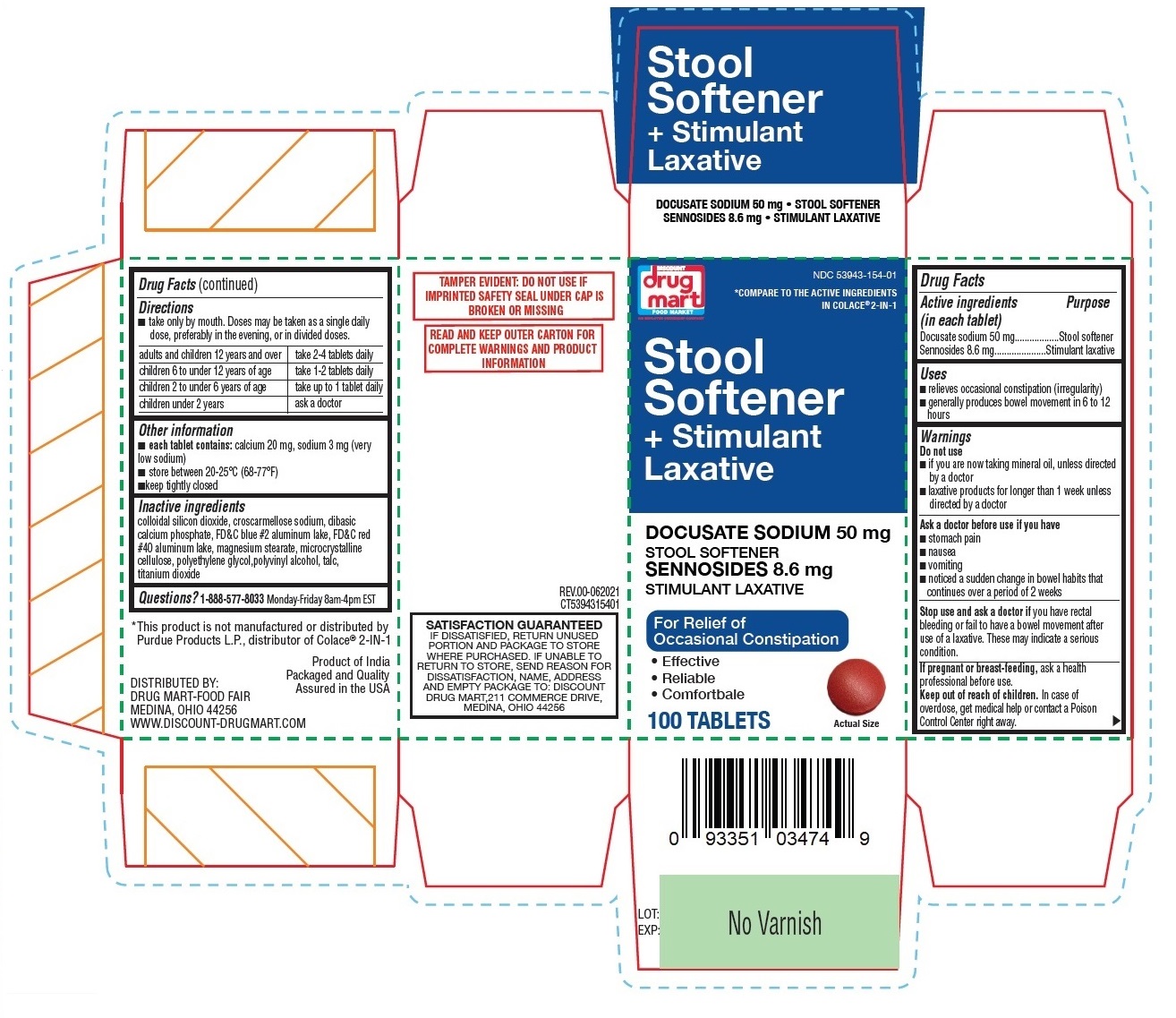 DRUG LABEL: Drug Mart Stool Softener plus Stimulant Laxative
NDC: 53943-154 | Form: TABLET
Manufacturer: Discount Drug Mart, Inc
Category: otc | Type: HUMAN OTC DRUG LABEL
Date: 20241213

ACTIVE INGREDIENTS: DOCUSATE SODIUM 50 mg/1 1; SENNOSIDES 8.6 mg/1 1
INACTIVE INGREDIENTS: SILICON DIOXIDE; CROSCARMELLOSE SODIUM; ANHYDROUS DIBASIC CALCIUM PHOSPHATE; FD&C BLUE NO. 2--ALUMINUM LAKE; FD&C RED NO. 40; MAGNESIUM STEARATE; MICROCRYSTALLINE CELLULOSE; POLYETHYLENE GLYCOL, UNSPECIFIED; POLYVINYL ALCOHOL, UNSPECIFIED; TALC; TITANIUM DIOXIDE

Drug Mart Stool Softener + Stimulant Laxative

Active ingredients (in each tablet)

Docusate sodium 50 mg

Sennosides 8.6 mg

Purpose

Stool softener

Stimulant Laxative

Uses

- relieves occasional constipation (irregularity)
- generally produces bowel movement in 6 to 12 hours

Warnings

Do not use

- if you are now taking mineral oil, unless directed by a doctor
- laxative products for longer than 1 week unless directed by a doctor

Ask a doctor before use if you have

- stomach pain
- nausea
- vomiting
- noticed a sudden change in bowel habits that continues over a period of 2 weeks

Stop use and ask a doctor if you have rectal bleeding or fail to have a bowel movement after use of a laxative. These may indicate a serious condition.

If pregnant or breast-feeding, ask a health professional before use.

Keep out of reach of children. In case of overdose, get medical help or contact a Poison Control Center right away.

Directions

- take only by mouth. Doses may be taken as a single daily dose, preferably in the evening, or in divided doses.

adults and children 12 years and over | take 2-4 tablets daily
children 6 to under 12 years of age | take 1-2 tablets daily
children 2 to under 6 years of age | take up to 1 tablet daily
children under 2 years | ask a doctor

Other information

- each tablet contains: calcium 20 mg, sodium 3 mg (very low sodium)
- store between 20-25°C (68-77°F)
- keep tightly closed

Inactive ingredients

colloidal silicon dioxide, croscarmellose sodium, dibasic calcium phosphate, FD&C blue #2 aluminum lake, FD&C red #40 aluminum lake, magnesium stearate, microcrystalline cellulose, polyethylene glycol, polyvinyl alcohol, talc, titanium dioxide

Questions?

1-888-577-8033 Monday-Friday 8am-4pm EST

COMPARE TO THE ACTIVE INGREDIENTS IN COLACE®2-IN-1

For Relief of Occasional Constipation

- Effective
- Reliable
- Comfortable

TAMPER EVIDENT: DO NOT USE IF PRINTED SAFETY SEAL UNDER CAP IS BROKEN OR MISSING

READ AND KEEP OUTER CARTON FOR COMPLETE PRODUCT INFORMATION

SATISFACTION GUARANTEED
IF DISSATISFIED, RETURN UNUSED PORTION AND PACKAGE TO STORE WHERE PURCHASED. IF UNABLE TO RETURN TO STORE, SEND REASON FOR DISSATISFACTION, NAME, ADDRESS AND EMPTY PACKAGE TO: DISCOUNT DRUG MART,211 COMMERCE DRIVE, MEDINA, OHIO 44256

* This product is not manufactured or distributed by Purdue Products L.P., distributor of Colace®2-IN-1.

DISTRIBUTED BY:
DRUG MART-FOOD FAIR
MEDINA, OHIO 44256
WWW.DISCOUNT-DRUGMART.COM

Product of India
Packaged and Quality Assured in the USA